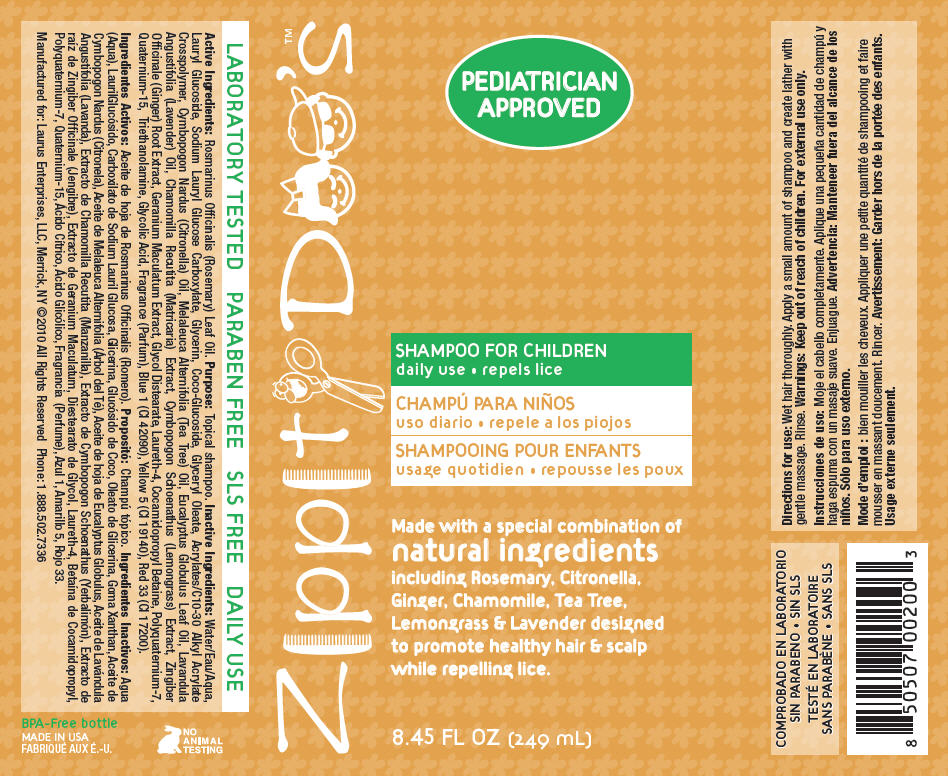 DRUG LABEL: Zippity Doos 
NDC: 57240-2003 | Form: SHAMPOO
Manufacturer: Laurus Enterprises, LLC
Category: homeopathic | Type: HUMAN OTC DRUG LABEL
Date: 20130227

ACTIVE INGREDIENTS: Rosemary Oil 2.49 mg/1 mL
INACTIVE INGREDIENTS: Water; Lauryl Glucoside; Glycerin; Coco Glucoside; Glyceryl Oleate; Citronella Oil; Eucalyptus Oil; Lavender Oil; Matricaria Recutita; Ginger; Geranium Maculatum Root; Glycol Distearate; Laureth-4; Cocamidopropyl Betaine; Quaternium-15; Trolamine; Glycolic Acid; FD&C Blue No. 1; FD&C Yellow No. 5; D&C Red No. 33

Zippity Doo's™
SHAMPOO FOR CHILDREN

Active Ingredients

Rosmarinus Officinalis (Rosemary) Leaf Oil.

Purpose

Topical shampoo.

Inactive Ingredients

Water/Eau/Aqua, Lauryl Glucoside, Sodium Lauryl Glucose Carboxylate, Glycerin, Coco-Glucoside, Glyceryl Oleate, Acrylates/C10-30 Alkyl Acrylate Crosspolymer, Cymbopogon Nardus (Citronella) Oil, Melaleuca Alternifolia (Tea Tree) Oil, Eucalyptus Globulus Leaf Oil, Lavandula Angustifolia (Lavender) Oil, Chamomilla Recutita (Matricaria) Extract, Cymbopogon Schoenathus (Lemongrass) Extract, Zingiber Officinale (Ginger) Root Extract, Geranium Maculatum Extract, Glycol Distearate, Laureth-4, Cocamidopropyl Betaine, Polyquaternium-7, Quaternium-15, Triethanolamine, Glycolic Acid, Fragrance (Parfum), Blue 1 (CI 42090), Yellow 5 (CI 19140), Red 33 (CI 17200).

Directions for use

INDICATIONS AND USAGE

Wet hair thoroughly. Apply a small amount of shampoo and create lather with gentle massage. Rinse.

Warnings

Keep out of reach of children. For external use only.

PRINCIPAL DISPLAY PANEL - 249 mL Bottle Label

Zippity Doo's™

PEDIATRICIAN
APPROVED

SHAMPOO FOR CHILDREN
daily use • repels lice

Made with a special combination of
natural ingredients
including Rosemary, Citronella,
Ginger, Chamomile, Tea Tree,
Lemongrass & Lavender designed
to promote healthy hair & scalp
while repelling lice.

8.45 FL OZ (249 mL)